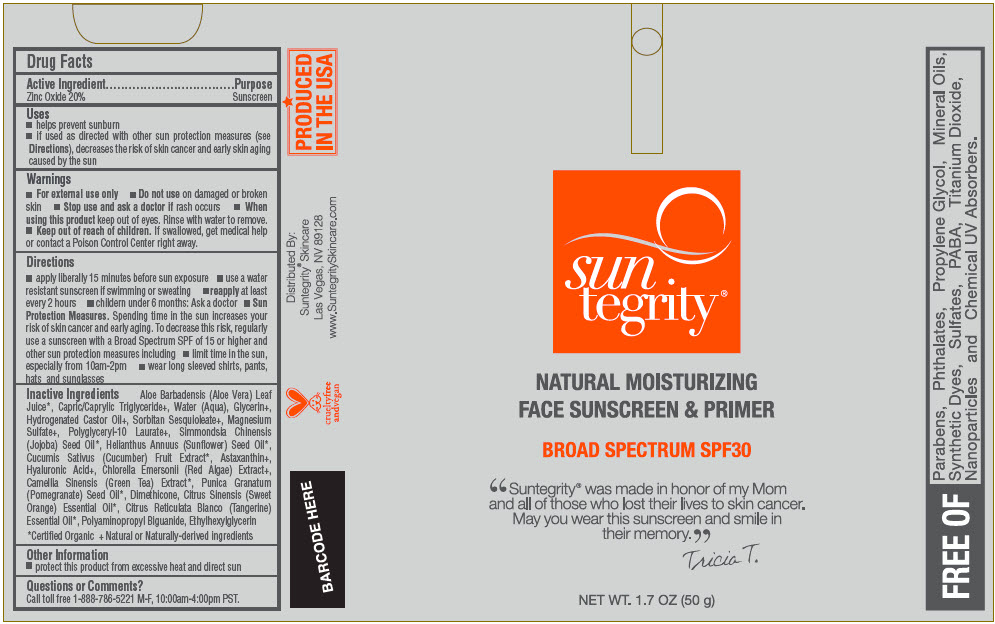 DRUG LABEL: NATURAL MOISTURIZING FACE SUNSCREEN and PRIMER
NDC: 69949-010 | Form: CREAM
Manufacturer: Synchronicity Spa, Inc. DBA Suntegrity
Category: otc | Type: HUMAN OTC DRUG LABEL
Date: 20241121

ACTIVE INGREDIENTS: Zinc Oxide 200 mg/1 g
INACTIVE INGREDIENTS: ALOE VERA LEAF; MEDIUM-CHAIN TRIGLYCERIDES; WATER; GLYCERIN; HYDROGENATED CASTOR OIL; SORBITAN SESQUIOLEATE; MAGNESIUM SULFATE, UNSPECIFIED FORM; POLYGLYCERYL-10 LAURATE; JOJOBA OIL; SUNFLOWER OIL; CUCUMBER; ASTAXANTHIN; HYALURONIC ACID; CHLORELLA EMERSONII; GREEN TEA LEAF; POMEGRANATE SEED OIL; DIMETHICONE; ORANGE OIL, COLD PRESSED; MANDARIN OIL; POLYAMINOPROPYL BIGUANIDE; ETHYLHEXYLGLYCERIN

NATURAL MOISTURIZING FACE SUNSCREEN & PRIMER

Drug Facts

Active Ingredient

Zinc Oxide 20%

Purpose

Sunscreen

Uses

- helps prevent sunburn
- if used as directed with other sun protection measures (see Directions), decreases the risk of skin cancer and early skin aging caused by the sun

Warnings

- For external use only
- Do not use on damaged or broken skin
- Stop use and ask a doctor if rash occurs
- When using this product keep out of eyes. Rinse with water to remove.

- Keep out of reach of children. If swallowed, get medical help or contact a Poison Control Center right away.

Directions

- apply liberally 15 minutes before sun exposure
- use a water resistant sunscreen if swimming or sweating
- reapply at least every 2 hours
- childern under 6 months: Ask a doctor
- Sun Protection Measures. Spending time in the sun increases your risk of skin cancer and early aging. To decrease this risk, regularly use a sunscreen with a Broad Spectrum SPF of 15 or higher and other sun protection measures including
  - limit time in the sun, especially from 10am-2pm
  - wear long sleeved shirts, pants, hats and sunglasses

Inactive Ingredients

Aloe Barbadensis (Aloe Vera) Leaf Juice [Certified Organic] , Capric/Caprylic Triglyceride [Natural or Naturally-derived ingredients] , Water (Aqua), Glycerin, Hydrogenated Castor Oil, Sorbitan Sesquioleate, Magnesium Sulfate, Polyglyceryl-10 Laurate, Simmondsia Chinensis (Jojoba) Seed Oil, Helianthus Annuus (Sunflower) Seed Oil, Cucumis Sativus (Cucumber) Fruit Extract, Astaxanthin, Hyaluronic Acid, Chlorella Emersonii (Red Algae) Extract, Camellia Sinensis (Green Tea) Extract, Punica Granatum (Pomegranate) Seed Oil, Dimethicone, Citrus Sinensis (Sweet Orange) Essential Oil, Citrus Reticulata Blanco (Tangerine) Essential Oil, Polyaminopropyl Biguanide, Ethylhexylglycerin

Other Information

- protect this product from excessive heat and direct sun

Questions or Comments?

Call toll free 1-888-786-5221 M-F, 10:00am-4:00pm PST.

Distributed By:
Suntegrity® Skincare
Las Vegas, NV 89128

PRINCIPAL DISPLAY PANEL - 50 g Canister Label

sun
tegrity®

NATURAL MOISTURIZING
FACE SUNSCREEN & PRIMER

BROAD SPECTRUM SPF30

"Suntegrity® was made in honor of my Mom
and all of those who lost their lives to skin cancer.
May you wear this sunscreen and smile in
their memory."

Tricia T.

NET WT. 1.7 OZ (50 g)